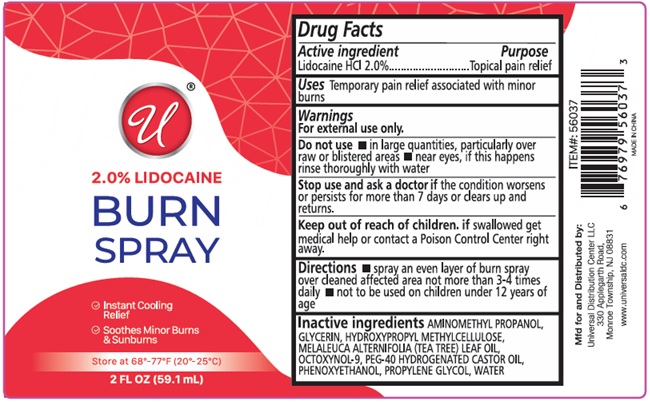 DRUG LABEL: 2.0% LIDOCAINE BURN
NDC: 43473-097 | Form: SPRAY
Manufacturer: Nantong Health & Beyond Hygienic Products Inc.
Category: otc | Type: HUMAN OTC DRUG LABEL
Date: 20260205

ACTIVE INGREDIENTS: LIDOCAINE HYDROCHLORIDE 2 g/100 mL
INACTIVE INGREDIENTS: AMINOMETHYLPROPANOL; GLYCERIN; HYPROMELLOSE, UNSPECIFIED; TEA TREE OIL; OCTOXYNOL-9; POLYOXYL 40 HYDROGENATED CASTOR OIL; PHENOXYETHANOL; PROPYLENE GLYCOL; WATER

43473-097 2.0% LIDOCAINE BURN SPRAY

Active ingredient

Lidocaine HCl 2.0%

Purpose

Topical pain relief

Uses

Temporary pain relief associated with minor burns

Warnings

For external use only.

Do not use • in large quantities, particularly over raw or blistered area • near eyes, if this happens rinse thoroughly with water

Stop use and ask a doctor if the condition worsens or persists for more than 7 days or clears up and returns.

Keep out of reach of children. if swallowed get medical help or contact a Poison Control Center right away.

Directions

• spray an even layer of burn spray over cleaned affected area not more than 3-4 times daily • not to be used on children under 12 years of age

Inactive ingredients

AMINOMETHYL PROPANOL, GLYCERIN, HYDROXYPROPYL METHYLCELLULOSE, MELALEUCA ALTERNIFOLIA (TEA TREE) LEAF OIL, OCTOXYNOL-9, PEG-40 HYDROGENATED CASTOR OIL, PHENOXYETHANOL, PROPYLENE GLYCOL, WATER

✓ Instant Cooling Relief

✓ Soothes Minor Burns & Sunburns

Store at 68°-77°F (20°-25°C)

Mfd for and Distributed by:
Universal Distribution Center LLC
330 Applegarth Road,
Monroe Township, NJ 08831

www.universaldc.com

MADE IN CHINA